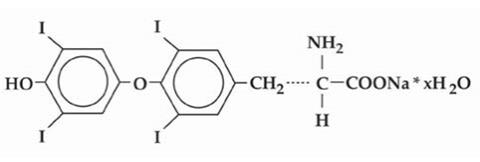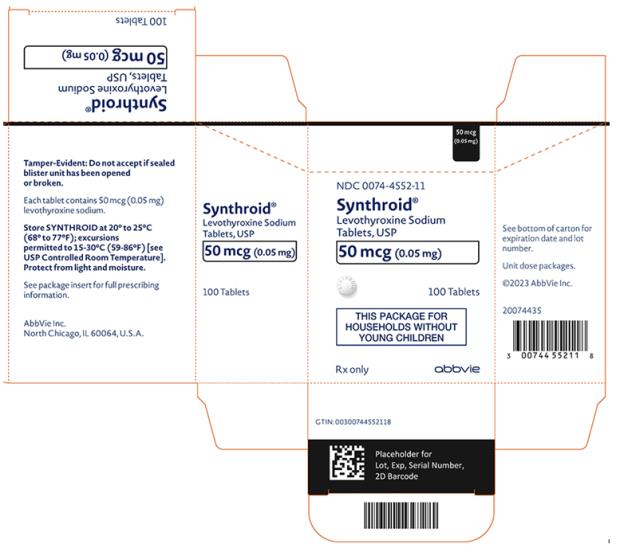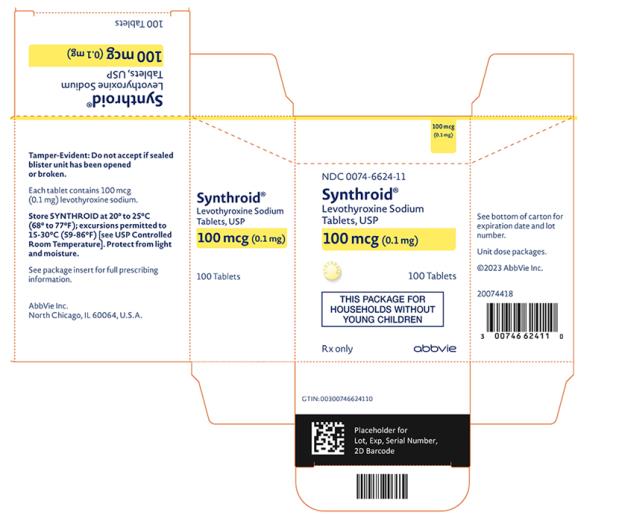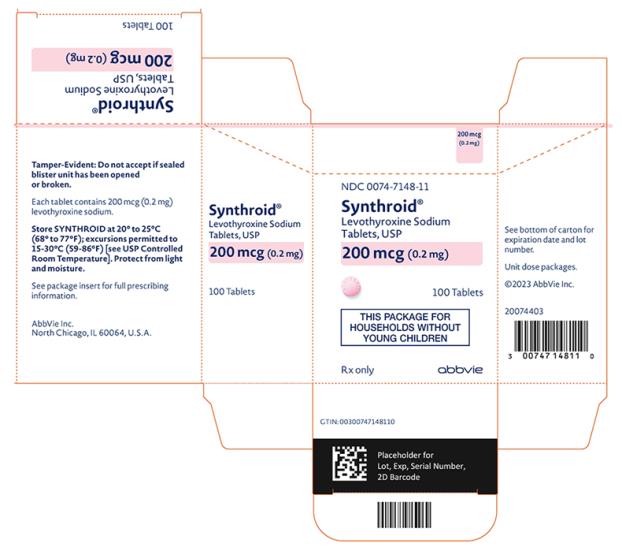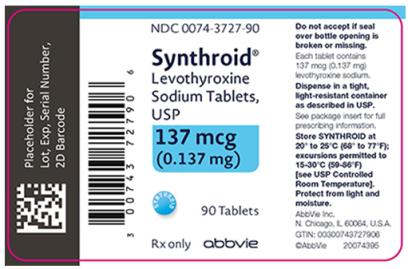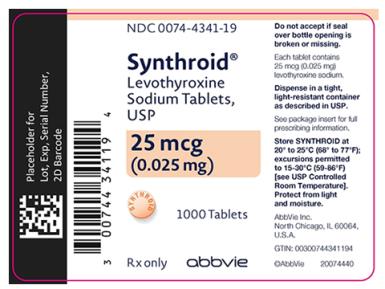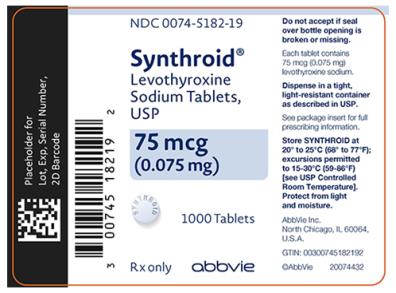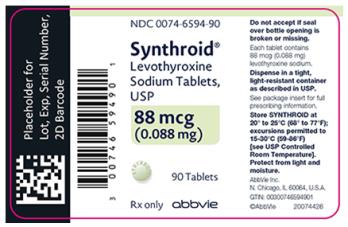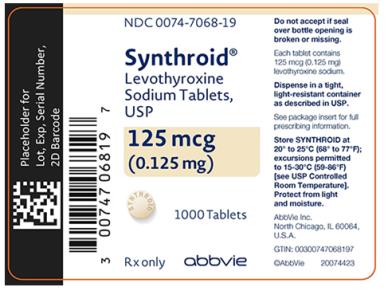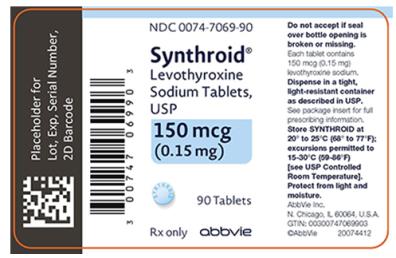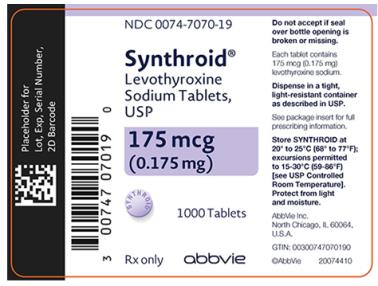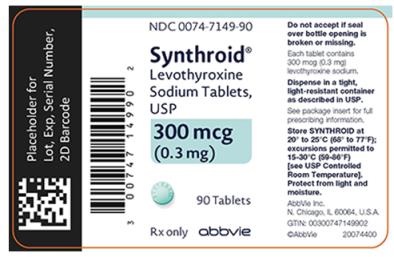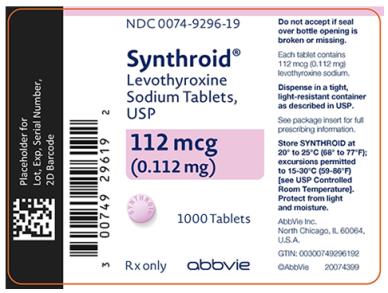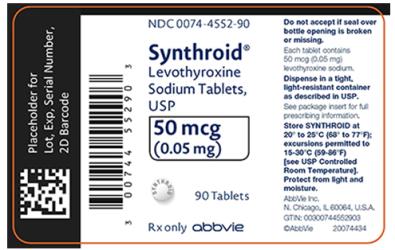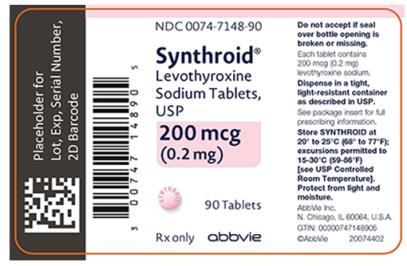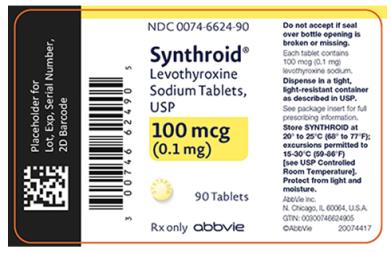 DRUG LABEL: Synthroid
NDC: 0074-4341 | Form: TABLET
Manufacturer: AbbVie Inc.
Category: prescription | Type: HUMAN PRESCRIPTION DRUG LABEL
Date: 20240220

ACTIVE INGREDIENTS: LEVOTHYROXINE SODIUM 25 ug/1 1
INACTIVE INGREDIENTS: ACACIA; LACTOSE MONOHYDRATE; MAGNESIUM STEARATE; POVIDONE, UNSPECIFIED; TALC; FD&C YELLOW NO. 6; SUCROSE

HIGHLIGHTS OF PRESCRIBING INFORMATION

These highlights do not include all the information needed to use SYNTHROID safely and effectively. See full prescribing information for SYNTHROID.
SYNTHROID® (levothyroxine sodium) tablets, for oral use
Initial U.S. Approval: 2002

RECENT MAJOR CHANGES

Dosage and Administration, Important Considerations for Dosing (2.2) | 2/2024
Dosage and Administration, Monitoring TSH and/or Thyroxine (T4) Levels (2.4) | 2/2024

WARNING: NOT FOR TREATMENT OF OBESITY OR FOR WEIGHT LOSS

See full prescribing information for complete boxed warning.

- Thyroid hormones, including SYNTHROID, should not be used for the treatment of obesity or for weight loss.
- Doses beyond the range of daily hormonal requirements may produce serious or even life-threatening manifestations of toxicity (6, 10).

1 INDICATIONS AND USAGE

SYNTHROID is a L-thyroxine (T4) indicated in adult and pediatric patients, including neonates, for:

- Hypothyroidism: As replacement therapy in primary (thyroidal), secondary (pituitary), and tertiary (hypothalamic) congenital or acquired hypothyroidism. (1)
- Pituitary Thyrotropin (Thyroid-Stimulating Hormone, TSH) Suppression: As an adjunct to surgery and radioiodine therapy in the management of thyrotropin-dependent well-differentiated thyroid cancer. (1)

Limitations of Use:

- Not indicated for suppression of benign thyroid nodules and nontoxic diffuse goiter in iodine-sufficient patients
- Not indicated for treatment of hypothyroidism during the recovery phase of subacute thyroiditis

2 DOSAGE AND ADMINISTRATION

- Administer once daily, preferably on an empty stomach, one-half to one hour before breakfast. (2.1)
- Administer at least 4 hours before or after drugs that are known to interfere with absorption. (2.1)
- Evaluate the need for dose adjustments when regularly administering within one hour of certain foods that may affect absorption. (2.1)
- Advise patients to stop biotin and biotin-containing supplements at least 2 days before assessing TSH and/or T4 levels. (2.2)
- Starting dose depends on a variety of factors, including age, body weight, cardiovascular status, and concomitant medications. Peak therapeutic effect may not be attained for 4-6 weeks. (2.2)
- See full prescribing information for dosing in specific patient populations. (2.3)
- Adequacy of therapy determined with periodic monitoring of TSH and/or T4 as well as clinical status. (2.4)

3 DOSAGE FORMS AND STRENGTHS

Tablets: 25, 50, 75, 88, 100, 112, 125, 137, 150, 175, 200, and 300 mcg (3)

4 CONTRAINDICATIONS

- Uncorrected adrenal insufficiency. (4)

5 WARNINGS AND PRECAUTIONS

- Serious risks related to overtreatment or undertreatment with SYNTHROID: Titrate the dose of SYNTHROID carefully and monitor response to titration. (5.1)
- Cardiac adverse reactions in the elderly and in patients with underlying cardiovascular disease: Initiate SYNTHROID at less than the full replacement dose because of the increased risk of cardiac adverse reactions, including atrial fibrillation. (2.3, 5.2, 8.5)
- Myxedema coma: Do not use oral thyroid hormone drug products to treat myxedema coma. (5.3)
- Acute adrenal crisis in patients with concomitant adrenal insufficiency: Treat with replacement glucocorticoids prior to initiation of SYNTHROID treatment. (5.4)
- Worsening of diabetic control: Therapy in patients with diabetes mellitus may worsen glycemic control and result in increased antidiabetic agent or insulin requirements. Carefully monitor glycemic control after starting, changing, or discontinuing thyroid hormone therapy. (5.5)
- Decreased bone mineral density associated with thyroid hormone over-replacement: Over-replacement can increase bone resorption and decrease bone mineral density. Give the lowest effective dose. (5.6)

6 ADVERSE REACTIONS

Adverse reactions associated with SYNTHROID therapy are primarily those of hyperthyroidism due to therapeutic overdosage: arrhythmias, myocardial infarction, dyspnea, muscle spasm, headache, nervousness, irritability, insomnia, tremors, muscle weakness, increased appetite, weight loss, diarrhea, heat intolerance, menstrual irregularities, and skin rash. (6)

To report SUSPECTED ADVERSE REACTIONS, contact AbbVie Inc. at 1-800-633-9110 or FDA at 1-800-FDA-1088 or www.fda.gov/medwatch.

7 DRUG INTERACTIONS

See full prescribing information for drugs that affect thyroid hormone pharmacokinetics and metabolism (e.g., absorption, synthesis, secretion, catabolism, protein binding, and target tissue response) and may alter the therapeutic response to SYNTHROID. (7)

8 USE IN SPECIFIC POPULATIONS

Pregnancy may require the use of higher doses of SYNTHROID. (2.3, 8.1)

FULL PRESCRIBING INFORMATION

WARNING: NOT FOR TREATMENT OF OBESITY OR FOR WEIGHT LOSS

Thyroid hormones, including SYNTHROID, either alone or with other therapeutic agents, should not be used for the treatment of obesity or for weight loss.

In euthyroid patients, doses within the range of daily hormonal requirements are ineffective for weight reduction.

Larger doses may produce serious or even life-threatening manifestations of toxicity, particularly when given in association with sympathomimetic amines such as those used for their anorectic effects [see Adverse Reactions (6), Drug Interactions (7.7), and Overdosage (10)].

1 INDICATIONS AND USAGE

Hypothyroidism

SYNTHROID is indicated in adult and pediatric patients, including neonates, as a replacement therapy in primary (thyroidal), secondary (pituitary), and tertiary (hypothalamic) congenital or acquired hypothyroidism.

Pituitary Thyrotropin (Thyroid-Stimulating Hormone, TSH) Suppression

SYNTHROID is indicated in adult and pediatric patients, including neonates, as an adjunct to surgery and radioiodine therapy in the management of thyrotropin-dependent well-differentiated thyroid cancer.

Limitations of Use

- SYNTHROID is not indicated for suppression of benign thyroid nodules and nontoxic diffuse goiter in iodine-sufficient patients as there are no clinical benefits and overtreatment with SYNTHROID may induce hyperthyroidism [see Warnings and Precautions (5.1)].
- SYNTHROID is not indicated for treatment of hypothyroidism during the recovery phase of subacute thyroiditis.

2 DOSAGE AND ADMINISTRATION

2.1 Important Administration Instructions

Administer SYNTHROID as a single daily dose, on an empty stomach, one-half to one hour before breakfast.

Administer SYNTHROID at least 4 hours before or after drugs known to interfere with SYNTHROID absorption [see Drug Interactions (7.1)].

Evaluate the need for dosage adjustments when regularly administering within one hour of certain foods that may affect SYNTHROID absorption [see Dosage and Administration (2.2 and 2.3), Drug Interactions (7.9), and Clinical Pharmacology (12.3)].

Administer SYNTHROID to pediatric patients who cannot swallow intact tablets by crushing the tablet, suspending the freshly crushed tablet in a small amount (5 to 10 mL) of water and immediately administering the suspension by spoon or dropper. Ensure the patient ingests the full amount of the suspension. Do not store the suspension. Do not administer in foods that decrease absorption of SYNTHROID, such as soybean-based infant formula [see Drug Interactions (7.9)].

2.2 Important Considerations for Dosing

The dosage of SYNTHROID for hypothyroidism or pituitary TSH suppression depends on a variety of factors including: the patient's age, body weight, cardiovascular status, concomitant medical conditions (including pregnancy), concomitant medications, co-administered food and the specific nature of the condition being treated [see Dosage and Administration (2.3), Warnings and Precautions (5), and Drug Interactions (7)]. Dosing must be individualized to account for these factors and dosage adjustments made based on periodic assessment of the patient's clinical response and laboratory parameters [see Dosage and Administration (2.4)].

For adult patients with primary hypothyroidism, titrate until the patient is clinically euthyroid and the serum TSH returns to normal [see Dosage and Administration (2.3)].

For secondary or tertiary hypothyroidism, serum TSH is not a reliable measure of SYNTHROID dosage adequacy and should not be used to monitor therapy. Use the serum free-T4 level to titrate SYNTHROID dosing until the patient is clinically euthyroid and the serum free-T4 level is restored to the upper half of the normal range [see Dosage and Administration (2.3)].

Inquire whether patients are taking biotin or biotin-containing supplements. If so, advise them to stop biotin supplementation at least 2 days before assessing TSH and/or T4 levels [see Dosage and Administration (2.4) and Drug Interactions (7.10)].

The peak therapeutic effect of a given dose of SYNTHROID may not be attained for 4 to 6 weeks.

2.3 Recommended Dosage and Titration

Primary, Secondary, and Tertiary Hypothyroidism in Adults

The recommended starting daily dosage of SYNTHROID in adults with primary, secondary, or tertiary hypothyroidism is based on age and comorbid cardiac conditions, as described in Table 1. For patients at risk of atrial fibrillation or patients with underlying cardiac disease, start with a lower dosage and titrate the dosage more slowly to avoid exacerbation of cardiac symptoms. Dosage titration is based on serum TSH or free-T4 [see Dosage and Administration (2.2)].

Table 1. SYNTHROID Dosing Guidelines for Hypothyroidism in Adults*
Patient Population | Starting Dosage | Dosage Titration Based on Serum TSH or Free-T4
Adults diagnosed with hypothyroidism | Full replacement dose is 1.6 mcg/kg/day. Some patients require a lower starting dose. | Titrate dosage by 12.5 to 25 mcg increments every 4 to 6 weeks, as needed until the patient is euthyroid.
Adults at risk for atrial fibrillation or with underlying cardiac disease | Lower starting dose (less than 1.6 mcg/kg/day) | Titrate dosage every 6 to 8 weeks, as needed until the patient is euthyroid.
Geriatric patients | Lower starting dose (less than 1.6 mcg/kg/day)

* Dosages greater than 200 mcg/day are seldom required. An inadequate response to daily dosages greater than 300 mcg/day is rare and may indicate poor compliance, malabsorption, drug interactions, or a combination of these factors [see Dosage and Administration (2.1) and Drug Interactions (7)].

Primary, Secondary, and Tertiary Hypothyroidism in Pediatric Patients

The recommended starting daily dosage of SYNTHROID in pediatric patients with primary, secondary, or tertiary hypothyroidism is based on body weight and changes with age as described in Table 2. Titrate the dosage (every 2 weeks) as needed based on serum TSH or free-T4 until the patient is euthyroid [see Dosage and Administration (2.2)].

Table 2. SYNTHROID Dosing Guidelines for Hypothyroidism in Pediatric Patients
Age | Starting Daily Dosage Per Kg Body Weight*
0-3 months | 10-15 mcg/kg/day
3-6 months | 8-10 mcg/kg/day
6-12 months | 6-8 mcg/kg/day
1-5 years | 5-6 mcg/kg/day
6-12 years | 4-5 mcg/kg/day
Greater than 12 years but growth and puberty incomplete | 2-3 mcg/kg/day
Growth and puberty complete | 1.6 mcg/kg/day
* Adjust dosage based on clinical response and laboratory parameters [see Dosage and Administration (2.4) and Use in Specific Populations (8.4)].

Pediatric Patients from Birth to 3 Months of Age at Risk for Cardiac Failure

Start at a lower starting dosage and increase the dosage every 4 to 6 weeks as needed based on clinical and laboratory response.

Pediatric Patients at Risk for Hyperactivity

To minimize the risk of hyperactivity, start at one-fourth the recommended full replacement dosage, and increase on a weekly basis by one-fourth the full recommended replacement dosage until the full recommended replacement dosage is reached.

Hypothyroidism in Pregnant Patients

For pregnant patients with pre-existing hypothyroidism, measure serum TSH and free-T4 as soon as pregnancy is confirmed and, at minimum, during each trimester of pregnancy. In pregnant patients with primary hypothyroidism, maintain serum TSH in the trimester-specific reference range.

The recommended daily dosage of SYNTHROID in pregnant patients is described in Table 3.

Table 3. SYNTHROID Dosing Guidelines for Hypothyroidism in Pregnant Patients
Patient Population | Starting Dosage | Dose Adjustment and Titration
Pre-existing primary hypothyroidism with serum TSH above normal trimester-specific range | Pre-pregnancy dosage may increase during pregnancy | Increase SYNTHROID dosage by 12.5 to 25 mcg per day. Monitor TSH every 4 weeks until a stable dose is reached and serum TSH is within normal trimester-specific range. Reduce SYNTHROID dosage to pre-pregnancy levels immediately after delivery. Monitor serum TSH 4 to 8 weeks postpartum.
New onset hypothyroidism (TSH ≥ 10 mIU per liter) | 1.6 mcg/kg/day | Monitor serum TSH every 4 weeks and adjust SYNTHROID dosage until serum TSH is within normal trimester-specific range.
New onset hypothyroidism (TSH < 10 mIU per liter) | 1.0 mcg/kg/day

TSH Suppression in Well-differentiated Thyroid Cancer in Adult and Pediatric Patients

The SYNTHROID dosage is based on the target level of TSH suppression for the stage and clinical status of thyroid cancer.

2.4 Monitoring TSH and/or Thyroxine (T4) Levels

Assess the adequacy of therapy by periodic assessment of laboratory tests and clinical evaluation.

Biotin supplementation may interfere with immunoassays for TSH, T4, and T3, resulting in erroneous thyroid hormone test results. Stop biotin and biotin-containing supplements for at least 2 days before assessing TSH and/or T4 levels [see Drug Interactions (7.10)].

Persistent clinical and laboratory evidence of hypothyroidism despite an apparent adequate replacement dose of SYNTHROID may be evidence of inadequate absorption, poor compliance, drug interactions, or a combination of these factors.

Adults

In adult patients with primary hypothyroidism, monitor serum TSH levels after an interval of 6 to 8 weeks after any change in dosage. In patients on a stable and appropriate replacement dosage, evaluate clinical and biochemical response every 6 to 12 months and whenever there is a change in the patient’s clinical status.

Pediatric Patients

In patients with hypothyroidism, assess the adequacy of replacement therapy by measuring both serum TSH and total or free-T4. Monitor TSH and total or free-T4 in pediatric patients as follows: 2 and 4 weeks after the initiation of treatment, 2 weeks after any change in dosage, and then every 3 to 12 months thereafter following dosage stabilization until growth is completed. Poor compliance or abnormal values may necessitate more frequent monitoring. Perform routine clinical examination, including assessment of development, mental and physical growth, and bone maturation, at regular intervals.

The general aim of therapy is to normalize the serum TSH level. TSH may not normalize in some patients due to in utero hypothyroidism causing a resetting of pituitary-thyroid feedback. Failure of the serum T4 to increase into the upper half of the normal range within 2 weeks of initiation of SYNTHROID therapy and/or of the serum TSH to decrease below 20 mIU per liter within 4 weeks may indicate the patient is not receiving adequate therapy. Assess compliance, dose of medication administered, and method of administration prior to increasing the dose of SYNTHROID [see Warnings and Precautions (5.1) and Use in Specific Populations (8.4)].

Secondary and Tertiary Hypothyroidism

Monitor serum free-T4 levels and maintain in the upper half of the normal range in these patients.

3 DOSAGE FORMS AND STRENGTHS

SYNTHROID tablets are available as follows (Table 4):

Table 4: SYNTHROID Tablet Strengths and Identifying Features
Tablet Strength | Tablet Color/Shape | Tablet Markings
25 mcg | Orange/Round | “SYNTHROID” and “25”
50 mcg | White/Round | “SYNTHROID” and “50”
75 mcg | Violet/Round | “SYNTHROID” and “75”
88 mcg | Olive/Round | “SYNTHROID” and “88”
100 mcg | Yellow/Round | “SYNTHROID” and “100”
112 mcg | Rose/Round | “SYNTHROID” and “112”
125 mcg | Brown/Round | “SYNTHROID” and “125”
137 mcg | Turquoise/Round | “SYNTHROID” and “137”
150 mcg | Blue/Round | “SYNTHROID” and “150”
175 mcg | Lilac/Round | “SYNTHROID” and “175”
200 mcg | Pink/Round | “SYNTHROID” and “200”
300 mcg | Green/Round | “SYNTHROID” and “300”

4 CONTRAINDICATIONS

SYNTHROID is contraindicated in patients with uncorrected adrenal insufficiency [see Warnings and Precautions (5.4)].

5 WARNINGS AND PRECAUTIONS

5.1 Serious Risks Related to Overtreatment or Undertreatment with SYNTHROID

SYNTHROID has a narrow therapeutic index. Overtreatment or undertreatment with SYNTHROID may have negative effects on growth and development, cardiovascular function, bone metabolism, reproductive function, cognitive function, gastrointestinal function, and glucose and lipid metabolism in adult or pediatric patients.

In pediatric patients with congenital and acquired hypothyroidism, undertreatment may adversely affect cognitive development and linear growth, and overtreatment is associated with craniosynostosis and acceleration of bone age [see Use in Specific Populations (8.4)].

Titrate the dose of SYNTHROID carefully and monitor response to titration to avoid these effects [see Dosage and Administration (2.4)]. Consider the potential for food or drug interactions and adjust the administration or dosage of SYNTHROID as needed [see Dosage and Administration (2.1), Drug Interactions (7.1), and Clinical Pharmacology (12.3)].

5.2 Cardiac Adverse Reactions in the Elderly and in Patients with Underlying Cardiovascular Disease

Over-treatment with levothyroxine may cause an increase in heart rate, cardiac wall thickness, and cardiac contractility and may precipitate angina or arrhythmias, particularly in patients with cardiovascular disease and in elderly patients. Initiate SYNTHROID therapy in this population at lower doses than those recommended in younger individuals or in patients without cardiac disease [see Dosage and Administration (2.3) and Use in Specific Populations (8.5)].

Monitor for cardiac arrhythmias during surgical procedures in patients with coronary artery disease receiving suppressive SYNTHROID therapy. Monitor patients receiving concomitant SYNTHROID and sympathomimetic agents for signs and symptoms of coronary insufficiency.

If cardiac symptoms develop or worsen, reduce the SYNTHROID dose or withhold for one week and restart at a lower dose.

5.3 Myxedema Coma

Myxedema coma is a life-threatening emergency characterized by poor circulation and hypometabolism and may result in unpredictable absorption of levothyroxine sodium from the gastrointestinal tract. Use of oral thyroid hormone drug products is not recommended to treat myxedema coma. Administer thyroid hormone products formulated for intravenous administration to treat myxedema coma.

5.4 Acute Adrenal Crisis in Patients with Concomitant Adrenal Insufficiency

Thyroid hormone increases metabolic clearance of glucocorticoids. Initiation of thyroid hormone therapy prior to initiating glucocorticoid therapy may precipitate an acute adrenal crisis in patients with adrenal insufficiency. Treat patients with adrenal insufficiency with replacement glucocorticoids prior to initiating treatment with SYNTHROID [see Contraindications (4)].

5.5 Worsening of Diabetic Control

Addition of levothyroxine therapy in patients with diabetes mellitus may worsen glycemic control and result in increased antidiabetic agent or insulin requirements. Carefully monitor glycemic control after starting, changing, or discontinuing SYNTHROID [see Drug Interactions (7.2)].

5.6 Decreased Bone Mineral Density Associated with Thyroid Hormone Over-Replacement

Increased bone resorption and decreased bone mineral density may occur as a result of levothyroxine over-replacement, particularly in post-menopausal women. The increased bone resorption may be associated with increased serum levels and urinary excretion of calcium and phosphorous, elevations in bone alkaline phosphatase, and suppressed serum parathyroid hormone levels. Administer the minimum dose of SYNTHROID that achieves the desired clinical and biochemical response to mitigate this risk.

6 ADVERSE REACTIONS

Adverse reactions associated with SYNTHROID therapy are primarily those of hyperthyroidism due to therapeutic overdosage [see Warnings and Precautions (5) and Overdosage (10)]. They include the following:

- General: fatigue, increased appetite, weight loss, heat intolerance, fever, excessive sweating
- Central nervous system: headache, hyperactivity, nervousness, anxiety, irritability, emotional lability, insomnia
- Musculoskeletal: tremors, muscle weakness, muscle spasm
- Cardiovascular: palpitations, tachycardia, arrhythmias, increased pulse and blood pressure, heart failure, angina, myocardial infarction, cardiac arrest
- Respiratory: dyspnea
- Gastrointestinal: diarrhea, vomiting, abdominal cramps, elevations in liver function tests
- Dermatologic: hair loss, flushing, rash
- Endocrine: decreased bone mineral density
- Reproductive: menstrual irregularities, impaired fertility

Seizures have been reported rarely with the institution of levothyroxine therapy.

Adverse Reactions in Pediatric Patients

Pseudotumor cerebri and slipped capital femoral epiphysis have been reported in pediatric patients receiving levothyroxine therapy. Overtreatment may result in craniosynostosis in infants who have not undergone complete closure of the fontanelles, and in premature closure of the epiphyses in pediatric patients still experiencing growth with resultant compromised adult height.

Hypersensitivity Reactions

Hypersensitivity reactions to inactive ingredients have occurred in patients treated with thyroid hormone products. These include urticaria, pruritus, skin rash, flushing, angioedema, various gastrointestinal symptoms (abdominal pain, nausea, vomiting and diarrhea), fever, arthralgia, serum sickness, and wheezing. Hypersensitivity to levothyroxine itself is not known to occur.

7 DRUG INTERACTIONS

7.1 Drugs Known to Affect Thyroid Hormone Pharmacokinetics

Many drugs can exert effects on thyroid hormone pharmacokinetics and metabolism (e.g., absorption, synthesis, secretion, catabolism, protein binding, and target tissue response) and may alter the therapeutic response to SYNTHROID (Tables 5 to 8).

Table 5. Drugs That May Decrease T4 Absorption (Hypothyroidism)
Potential impact: Concurrent use may reduce the efficacy of SYNTHROID by binding and delaying or preventing absorption, potentially resulting in hypothyroidism.
Drug or Drug Class | Effect
Phosphate Binders (e.g., calcium carbonate, ferrous sulfate, sevelamer, lanthanum) | Phosphate binders may bind to levothyroxine. Administer SYNTHROID at least 4 hours apart from these agents.
Orlistat | Monitor patients treated concomitantly with orlistat and SYNTHROID for changes in thyroid function.
Bile Acid Sequestrants (e.g., colesevelam, cholestyramine, colestipol) Ion Exchange Resins (e.g., Kayexalate) | Bile acid sequestrants and ion exchange resins are known to decrease levothyroxine absorption. Administer SYNTHROID at least 4 hours prior to these drugs or monitor TSH levels.
Proton Pump Inhibitors Sucralfate Antacids (e.g., aluminum & magnesium hydroxides, simethicone) | Gastric acidity is an essential requirement for adequate absorption of levothyroxine. Sucralfate, antacids and proton pump inhibitors may cause hypochlorhydria, affect intragastric pH, and reduce levothyroxine absorption. Monitor patients appropriately.

Table 6. Drugs That May Alter T4 and Triiodothyronine (T3) Serum Transport Without Affecting Free Thyroxine (FT4) Concentration (Euthyroidism)
Drug or Drug Class | Effect
Clofibrate Estrogen-containing oral contraceptives Estrogens (oral) Heroin / Methadone 5-Fluorouracil Mitotane Tamoxifen | These drugs may increase serum thyroxine-binding globulin (TBG) concentration.
Androgens / Anabolic Steroids Asparaginase Glucocorticoids Slow-Release Nicotinic Acid | These drugs may decrease serum TBG concentration.
Potential impact (below): Administration of these agents with SYNTHROID results in an initial transient increase in FT4. Continued administration results in a decrease in serum T4 and normal FT4 and TSH concentrations.
Salicylates (> 2 g/day) | Salicylates inhibit binding of T4 and T3 to TBG and transthyretin. An initial increase in serum FT4 is followed by return of FT4 to normal levels with sustained therapeutic serum salicylate concentrations, although total T4 levels may decrease by as much as 30%.
Other drugs: Carbamazepine Furosemide (> 80 mg IV) Heparin Hydantoins Non-Steroidal Anti-inflammatory Drugs - Fenamates | These drugs may cause protein-binding site displacement. Furosemide has been shown to inhibit the protein binding of T4 to TBG and albumin, causing an increase free T4 fraction in serum. Furosemide competes for T4-binding sites on TBG, prealbumin, and albumin, so that a single high dose can acutely lower the total T4 level. Phenytoin and carbamazepine reduce serum protein binding of levothyroxine, and total and free T4 may be reduced by 20% to 40%, but most patients have normal serum TSH levels and are clinically euthyroid. Closely monitor thyroid hormone parameters.

Table 7. Drugs That May Alter Hepatic Metabolism of T4 (Hypothyroidism)
Potential impact: Stimulation of hepatic microsomal drug-metabolizing enzyme activity may cause increased hepatic degradation of levothyroxine, resulting in increased SYNTHROID requirements.
Drug or Drug Class | Effect
Phenobarbital Rifampin | Phenobarbital has been shown to reduce the response to thyroxine. Phenobarbital increases L-thyroxine metabolism by inducing uridine 5’-diphospho-glucuronosyltransferase (UGT) and leads to lower T4 serum levels. Changes in thyroid status may occur if barbiturates are added or withdrawn from patients being treated for hypothyroidism. Rifampin has been shown to accelerate the metabolism of levothyroxine.

Table 8. Drugs That May Decrease Conversion of T4 to T3
Potential impact: Administration of these enzyme inhibitors decreases the peripheral conversion of T4 to T3, leading to decreased T3 levels. However, serum T4 levels are usually normal but may occasionally be slightly increased.
Drug or Drug Class | Effect
Beta-adrenergic antagonists (e.g., Propranolol > 160 mg/day) | In patients treated with large doses of propranolol (> 160 mg/day), T3 and T4 levels change, TSH levels remain normal, and patients are clinically euthyroid. Actions of particular beta-adrenergic antagonists may be impaired when a hypothyroid patient is converted to the euthyroid state.
Glucocorticoids (e.g., Dexamethasone > 4 mg/day) | Short-term administration of large doses of glucocorticoids may decrease serum T3 concentrations by 30% with minimal change in serum T4 levels. However, long-term glucocorticoid therapy may result in slightly decreased T3 and T4 levels due to decreased TBG production (See above).
Other drugs: Amiodarone | Amiodarone inhibits peripheral conversion of levothyroxine (T4) to triiodothyronine (T3) and may cause isolated biochemical changes (increase in serum free-T4, and decreased or normal free-T3) in clinically euthyroid patients.

7.2 Antidiabetic Therapy

Addition of SYNTHROID therapy in patients with diabetes mellitus may worsen glycemic control and result in increased antidiabetic agent or insulin requirements. Carefully monitor glycemic control, especially when thyroid therapy is started, changed, or discontinued [see Warnings and Precautions (5.5)].

7.3 Oral Anticoagulants

SYNTHROID increases the response to oral anticoagulant therapy. Therefore, a decrease in the dose of anticoagulant may be warranted with correction of the hypothyroid state or when the SYNTHROID dose is increased. Closely monitor coagulation tests to permit appropriate and timely dosage adjustments.

7.4 Digitalis Glycosides

SYNTHROID may reduce the therapeutic effects of digitalis glycosides. Serum digitalis glycoside levels may decrease when a hypothyroid patient becomes euthyroid, necessitating an increase in the dose of digitalis glycosides.

7.5 Antidepressant Therapy

Concurrent use of tricyclic (e.g., amitriptyline) or tetracyclic (e.g., maprotiline) antidepressants and SYNTHROID may increase the therapeutic and toxic effects of both drugs, possibly due to increased receptor sensitivity to catecholamines. Toxic effects may include increased risk of cardiac arrhythmias and central nervous system stimulation. SYNTHROID may accelerate the onset of action of tricyclics. Administration of sertraline in patients stabilized on SYNTHROID may result in increased SYNTHROID requirements.

7.6 Ketamine

Concurrent use of ketamine and SYNTHROID may produce marked hypertension and tachycardia. Closely monitor blood pressure and heart rate in these patients.

7.7 Sympathomimetics

Concurrent use of sympathomimetics and SYNTHROID may increase the effects of sympathomimetics or thyroid hormone. Thyroid hormones may increase the risk of coronary insufficiency when sympathomimetic agents are administered to patients with coronary artery disease.

7.8 Tyrosine-Kinase Inhibitors

Concurrent use of tyrosine-kinase inhibitors such as imatinib may cause hypothyroidism. Closely monitor TSH levels in such patients.

7.9 Drug-Food Interactions

Consumption of certain foods may affect SYNTHROID absorption thereby necessitating adjustments in dosing [see Dosage and Administration (2.1)]. Soybean flour, cottonseed meal, walnuts, and dietary fiber may bind and decrease the absorption of SYNTHROID from the gastrointestinal tract. Grapefruit juice may delay the absorption of levothyroxine and reduce its bioavailability.

7.10 Drug-Laboratory Test Interactions

Thyroxine-binding Globulin (TBG)

Consider changes in TBG concentration when interpreting T4 and T3 values. Measure and evaluate unbound (free) hormone and/or determine the free-T4 index (FT4I) in this circumstance. Pregnancy, infectious hepatitis, estrogens, estrogen-containing oral contraceptives, and acute intermittent porphyria increase TBG concentration. Nephrosis, severe hypoproteinemia, severe liver disease, acromegaly, androgens, and corticosteroids decrease TBG concentration. Familial hyper- or hypo-thyroxine binding globulinemias have been described, with the incidence of TBG deficiency approximating 1 in 9000.

Biotin

Biotin supplementation is known to interfere with thyroid hormone immunoassays that are based on a biotin and streptavidin interaction, which may result in erroneous thyroid hormone test results. Stop biotin and biotin-containing supplements for at least 2 days prior to thyroid testing.

8 USE IN SPECIFIC POPULATIONS

8.1 Pregnancy

Risk Summary

The clinical experience, including data from postmarketing studies, in pregnant women treated with oral levothyroxine to maintain euthyroid state have not reported increased rates of major birth defects, miscarriages, or other adverse maternal or fetal outcomes. There are risks to the mother and fetus associated with untreated hypothyroidism in pregnancy. Since TSH levels may increase during pregnancy, TSH should be monitored and SYNTHROID dosage adjusted during pregnancy (see Clinical Considerations). Animal reproductive studies have not been conducted with levothyroxine sodium. SYNTHROID should not be discontinued during pregnancy and hypothyroidism diagnosed during pregnancy should be promptly treated.

The estimated background risk of major birth defects and miscarriage for the indicated population is unknown. All pregnancies have a background risk of birth defect, loss, or other adverse outcomes. In the U.S. general population, the estimated background risk of major birth defects and miscarriage in clinically recognized pregnancies is 2% to 4% and 15% to 20%, respectively.

Clinical Considerations

Disease-Associated Maternal and/or Embryo/Fetal Risk

Maternal hypothyroidism during pregnancy is associated with a higher rate of complications, including spontaneous abortion, gestational hypertension, pre-eclampsia, stillbirth, and premature delivery. Untreated maternal hypothyroidism may have an adverse effect on fetal neurocognitive development.

Dose Adjustments During Pregnancy and the Postpartum Period

Pregnancy may increase SYNTHROID requirements. Serum TSH levels should be monitored and the SYNTHROID dosage adjusted during pregnancy. Since postpartum TSH levels are similar to preconception values, the SYNTHROID dosage should return to the pre-pregnancy dose immediately after delivery [see Dosage and Administration (2.3)].

8.2 Lactation

Risk Summary

Published studies report that levothyroxine is present in human milk following the administration of oral levothyroxine. No adverse effects on the breastfed infant have been reported and there is no information on the effects of levothyroxine on milk production. Adequate levothyroxine treatment during lactation may normalize milk production in hypothyroid lactating mothers with low milk supply. The developmental and health benefits of breastfeeding should be considered along with the mother’s clinical need for SYNTHROID and any potential adverse effects on the breastfed infant from SYNTHROID or from the underlying maternal condition.

8.4 Pediatric Use

SYNTHROID is indicated in patients from birth to less than 17 years of age:

- As a replacement therapy in primary (thyroidal), secondary (pituitary), and tertiary (hypothalamic) congenital or acquired hypothyroidism.
- As an adjunct to surgery and radioiodine therapy in the management of thyrotropin-dependent well-differentiated thyroid cancer.

Rapid restoration of normal serum T4 concentrations is essential for preventing the adverse effects of congenital hypothyroidism on cognitive development as well as on overall physical growth and maturation. Therefore, initiate SYNTHROID therapy immediately upon diagnosis. Levothyroxine is generally continued for life in these patients [see Warnings and Precautions (5.1)].

Closely monitor infants during the first 2 weeks of SYNTHROID therapy for cardiac overload and arrhythmias.

8.5 Geriatric Use

Because of the increased prevalence of cardiovascular disease among the elderly, initiate SYNTHROID at less than the full replacement dose [see Dosage and Administration (2.3) and Warnings and Precautions (5.2)]. Atrial arrhythmias can occur in elderly patients. Atrial fibrillation is the most common of the arrhythmias observed with levothyroxine overtreatment in the elderly.

10 OVERDOSAGE

The signs and symptoms of overdosage are those of hyperthyroidism [see Warnings and Precautions (5) and Adverse Reactions (6)]. In addition, confusion and disorientation may occur. Cerebral embolism, shock, coma, and death have been reported. Seizures occurred in a 3-year-old child ingesting 3.6 mg of levothyroxine. Symptoms may not necessarily be evident or may not appear until several days after ingestion of levothyroxine sodium.

Reduce the SYNTHROID dosage or discontinue temporarily if signs or symptoms of overdosage occur. Initiate appropriate supportive treatment as dictated by the patient’s medical status.

For current information on the management of poisoning or overdosage, contact the National Poison Control Center at 1-800-222-1222 or www.poison.org.

11 DESCRIPTION

SYNTHROID (levothyroxine sodium tablets, USP) is L-thyroxine (T4) and contains synthetic crystalline L-3,3',5,5'-tetraiodothyronine sodium salt. Synthetic T4 is chemically identical to that produced in the human thyroid gland. Levothyroxine (T4) sodium has an empirical formula of C15H10I4N NaO4• H2O, molecular weight of 798.86 (anhydrous), and structural formula as shown:

SYNTHROID tablets for oral administration are supplied in the following strengths: 25 mcg, 50 mcg, 75 mcg, 88 mcg, 100 mcg, 112 mcg, 125 mcg, 137 mcg, 150 mcg, 175 mcg, 200 mcg, and 300 mcg. Each SYNTHROID tablet contains the inactive ingredients acacia, confectioner's sugar (contains corn starch), lactose monohydrate, magnesium stearate, povidone, and talc. SYNTHROID tablets contain no ingredients made from a gluten-containing grain (wheat, barley, or rye). Each tablet strength meets USP Dissolution Test 3. Table 9 provides a listing of the color additives by tablet strength:

Table 9: SYNTHROID Tablet Color Additives
Strength (mcg) | Color additive(s)
25 | FD&C Yellow No. 6 Aluminum Lake*
50 | None
75 | FD&C Red No. 40 Aluminum Lake, FD&C Blue No. 2 Aluminum Lake
88 | FD&C Blue No. 1 Aluminum Lake, FD&C Yellow No. 6 Aluminum Lake*, D&C Yellow No. 10 Aluminum Lake
100 | D&C Yellow No. 10 Aluminum Lake, FD&C Yellow No. 6 Aluminum Lake*
112 | D&C Red No. 27 & 30 Aluminum Lake
125 | FD&C Yellow No. 6 Aluminum Lake*, FD&C Red No. 40 Aluminum Lake, FD&C Blue No. 1 Aluminum Lake
137 | FD&C Blue No. 1 Aluminum Lake
150 | FD&C Blue No. 2 Aluminum Lake
175 | FD&C Blue No. 1 Aluminum Lake, D&C Red No. 27 & 30 Aluminum Lake
200 | FD&C Red No. 40 Aluminum Lake
300 | D&C Yellow No. 10 Aluminum Lake, FD&C Yellow No. 6 Aluminum Lake*, FD&C Blue No. 1 Aluminum Lake
* Note – FD&C Yellow No. 6 is orange in color.

12 CLINICAL PHARMACOLOGY

12.1 Mechanism of Action

Thyroid hormones exert their physiologic actions through control of DNA transcription and protein synthesis. Triiodothyronine (T3) and L-thyroxine (T4) diffuse into the cell nucleus and bind to thyroid receptor proteins attached to DNA. This hormone nuclear receptor complex activates gene transcription and synthesis of messenger RNA and cytoplasmic proteins.

The physiological actions of thyroid hormones are produced predominantly by T3, the majority of which (approximately 80%) is derived from T4 by deiodination in peripheral tissues.

12.2 Pharmacodynamics

Oral levothyroxine sodium is a synthetic T4 hormone that exerts the same physiologic effect as endogenous T4, thereby maintaining normal T4 levels when a deficiency is present.

12.3 Pharmacokinetics

Absorption

Absorption of orally administered T4 from the gastrointestinal tract ranges from 40% to 80%. The majority of the SYNTHROID dose is absorbed from the jejunum and upper ileum. The relative bioavailability of SYNTHROID tablets, compared to an equal nominal dose of oral levothyroxine sodium solution, is approximately 93%. T4 absorption is increased by fasting, and decreased in malabsorption syndromes and by certain foods such as soybeans. Dietary fiber decreases bioavailability of T4. Absorption may also decrease with age. In addition, many drugs and foods affect T4 absorption [see Drug Interactions (7)].

Distribution

Circulating thyroid hormones are greater than 99% bound to plasma proteins, including thyroxine-binding globulin (TBG), thyroxine-binding prealbumin (TBPA), and albumin (TBA), whose capacities and affinities vary for each hormone. The higher affinity of both TBG and TBPA for T4 partially explains the higher serum levels, slower metabolic clearance, and longer half-life of T4 compared to T3. Protein-bound thyroid hormones exist in reverse equilibrium with small amounts of free hormone. Only unbound hormone is metabolically active. Many drugs and physiologic conditions affect the binding of thyroid hormones to serum proteins [see Drug Interactions (7)]. Thyroid hormones do not readily cross the placental barrier [see Use in Specific Populations (8.1)].

Elimination

Metabolism

T4 is slowly eliminated (see Table 10). The major pathway of thyroid hormone metabolism is through sequential deiodination. Approximately 80% of circulating T3 is derived from peripheral T4 by monodeiodination. The liver is the major site of degradation for both T4 and T3, with T4 deiodination also occurring at a number of additional sites, including the kidney and other tissues. Approximately 80% of the daily dose of T4 is deiodinated to yield equal amounts of T3 and reverse T3 (rT3). T3 and rT3 are further deiodinated to diiodothyronine. Thyroid hormones are also metabolized via conjugation with glucuronides and sulfates and excreted directly into the bile and gut where they undergo enterohepatic recirculation.

Excretion

Thyroid hormones are primarily eliminated by the kidneys. A portion of the conjugated hormone reaches the colon unchanged and is eliminated in the feces. Approximately 20% of T4 is eliminated in the stool. Urinary excretion of T4 decreases with age.

Table 10. Pharmacokinetic Parameters of Thyroid Hormones in Euthyroid Patients
Hormone | Ratio in Thyroglobulin | Biologic Potency | t 1/2 (days) | Protein Binding (%)*
Levothyroxine (T4) | 10 - 20 | 1 | 6-7** | 99.96
Liothyronine (T3) | 1 | 4 | ≤ 2 | 99.5
* Includes TBG, TBPA, and TBA
** 3 to 4 days in hyperthyroidism, 9 to 10 days in hypothyroidism

13 NONCLINICAL TOXICOLOGY

13.1 Carcinogenesis, Mutagenesis, Impairment of Fertility

Long-term carcinogenicity studies in animals to evaluate the carcinogenic potential of levothyroxine have not been performed. Studies to evaluate mutagenic potential and animal fertility have not been performed.

16 HOW SUPPLIED/STORAGE AND HANDLING

How Supplied

SYNTHROID (levothyroxine sodium, USP) tablets are supplied as follows (Table 11):

Table 11: SYNTHROID Tablet Presentations
Strength (mcg) | Color/Shape | Tablet Markings | NDC# for bottles of 90 | NDC # for bottles of 1000 | NDC # for unit dose cartons of 100
25 | Orange/Round | “SYNTHROID” and “25” | 0074-4341-90 | 0074-4341-19 | --
50 | White/Round | “SYNTHROID” and “50” | 0074-4552-90 | 0074-4552-19 | 0074-4552-11
75 | Violet/Round | “SYNTHROID” and “75” | 0074-5182-90 | 0074-5182-19 | 0074-5182-11
88 | Olive/Round | “SYNTHROID” and “88” | 0074-6594-90 | 0074-6594-19 | --
100 | Yellow/Round | “SYNTHROID” and “100” | 0074-6624-90 | 0074-6624-19 | 0074-6624-11
112 | Rose/Round | “SYNTHROID” and “112” | 0074-9296-90 | 0074-9296-19 | --
125 | Brown/Round | “SYNTHROID” and “125” | 0074-7068-90 | 0074-7068-19 | 0074-7068-11
137 | Turquoise/Round | “SYNTHROID” and “137” | 0074-3727-90 | 0074-3727-19 | --
150 | Blue/Round | “SYNTHROID” and “150” | 0074-7069-90 | 0074-7069-19 | 0074-7069-11
175 | Lilac/Round | “SYNTHROID” and “175” | 0074-7070-90 | 0074-7070-19 | --
200 | Pink/Round | “SYNTHROID” and “200” | 0074-7148-90 | 0074-7148-19 | 0074-7148-11
300 | Green/Round | “SYNTHROID” and “300” | 0074-7149-90 | 0074-7149-19 | --

Storage and Handling

Store SYNTHROID at 20° to 25°C (68° to 77°F); excursions permitted to 15° to 30°C (59° to 86°F) (see USP Controlled Room Temperature).

SYNTHROID tablets should be protected from light and moisture.

17 PATIENT COUNSELING INFORMATION

Inform the patient of the following information to aid in the safe and effective use of SYNTHROID:

Dosing and Administration

- Instruct patients to take SYNTHROID only as directed by their healthcare provider.
- Instruct patients to take SYNTHROID as a single dose, preferably on an empty stomach, one-half to one hour before breakfast.
- Inform patients that agents such as iron and calcium supplements and antacids can decrease the absorption of levothyroxine. Instruct patients not to take SYNTHROID tablets within 4 hours of these agents.
- Instruct patients to notify their healthcare provider if they are pregnant or breastfeeding or are thinking of becoming pregnant while taking SYNTHROID.

Important Information

- Inform patients that it may take several weeks before they notice an improvement in symptoms.
- Inform patients that the levothyroxine in SYNTHROID is intended to replace a hormone that is normally produced by the thyroid gland. Generally, replacement therapy is to be taken for life.
- Inform patients that SYNTHROID should not be used as a primary or adjunctive therapy in a weight control program.
- Instruct patients to notify their healthcare provider if they are taking any other medications, including prescription and over-the-counter preparations.
- Instruct patients to discontinue biotin or any biotin-containing supplements for at least 2 days before thyroid function testing is conducted.
- Instruct patients to notify their physician of any other medical conditions they may have, particularly heart disease, diabetes, clotting disorders, and adrenal or pituitary gland problems, as the dose of medications used to control these other conditions may need to be adjusted while they are taking SYNTHROID. If they have diabetes, instruct patients to monitor their blood and/or urinary glucose levels as directed by their physician and immediately report any changes to their physician. If patients are taking anticoagulants, their clotting status should be checked frequently.
- Instruct patients to notify their physician or dentist that they are taking SYNTHROID prior to any surgery.

Adverse Reactions

- Instruct patients to notify their healthcare provider if they experience any of the following symptoms: rapid or irregular heartbeat, chest pain, shortness of breath, leg cramps, headache, nervousness, irritability, sleeplessness, tremors, change in appetite, weight gain or loss, vomiting, diarrhea, excessive sweating, heat intolerance, fever, changes in menstrual periods, hives or skin rash, or any other unusual medical event.
- Inform patients that partial hair loss may occur rarely during the first few months of SYNTHROID therapy, but this is usually temporary.

© 2024 AbbVie Inc. All rights reserved.

SYNTHROID and its design are trademarks of AbbVie Inc.

AbbVie Inc.

North Chicago, IL 60064 U.S.A.

20083657

PACKAGE LABEL

NDC 0074-4552-11

Synthroid®

Levothyroxine Sodium
Tablets, USP

50 mcg (0.05 mg)

100 Tablets

THIS PACKAGE FOR
HOUSEHOLDS WITHOUT
YOUNG CHILDREN

Rx only abbvie

PACKAGE LABEL

NDC 0074-6624-11

Synthroid®

Levothyroxine Sodium
Tablets, USP

100 mcg (0.1 mg)

100 Tablets

THIS PACKAGE FOR
HOUSEHOLDS WITHOUT
YOUNG CHILDREN

Rx only abbvie

PACKAGE LABEL

NDC 0074-7148-11

Synthroid®

Levothyroxine Sodium
Tablets, USP

200 mcg (0.2 mg)

100 Tablets

THIS PACKAGE FOR
HOUSEHOLDS WITHOUT
YOUNG CHILDREN

Rx only abbvie

PACKAGE LABEL

NDC 0074-3727-90

Synthroid®

Levothyroxine
Sodium Tablets,
USP

137 mcg
(0.137 mg)

90 Tablets

Rx only abbvie

PACKAGE LABEL

NDC 0074-4341-19

Synthroid®

Levothyroxine
Sodium Tablets,
USP

25 mcg
(0.025 mg)

1000 Tablets

Rx only abbvie

PACKAGE LABEL

NDC 0074-5182-19

Synthroid®

Levothyroxine
Sodium Tablets,
USP

75 mcg
(0.075 mg)

1000 Tablets

Rx only abbvie

PACKAGE LABEL

NDC 0074-6594-90

Synthroid®

Levothyroxine
Sodium Tablets,
USP

88 mcg
(0.088 mg)

90 Tablets

Rx only abbvie

PACKAGE LABEL

NDC 0074-7068-19

Synthroid®

Levothyroxine
Sodium Tablets,
USP

125 mcg
(0.125 mg)

1000 Tablets

Rx only abbvie

PACKAGE LABEL

NDC 0074-7069-90

Synthroid®

Levothyroxine
Sodium Tablets,
USP

150 mcg
(0.15 mg)

90 Tablets

Rx only abbvie

PACKAGE LABEL

NDC 0074-7070-19

Synthroid®

Levothyroxine
Sodium Tablets,
USP

175 mcg
(0.175 mg)

1000 Tablets

Rx only abbvie

PACKAGE LABEL

NDC 0074-7149-90

Synthroid®

Levothyroxine
Sodium Tablets,
USP

300 mcg
(0.3 mg)

90 Tablets

Rx only abbvie

PACKAGE LABEL

NDC 0074-9296-19

Synthroid®

Levothyroxine
Sodium Tablets,
USP

112 mcg
(0.112 mg)

1000 Tablets

Rx only abbvie

PACKAGE LABEL

NDC 0074-4552-90

Synthroid®

Levothyroxine
Sodium Tablets,
USP

50 mcg
(0.05 mg)

90 Tablets

Rx only abbvie

PACKAGE LABEL

NDC 0074-7148-90

Synthroid®

Levothyroxine
Sodium Tablets,
USP

200 mcg
(0.2 mg)

90 Tablets

Rx only abbvie

PACKAGE LABEL

NDC 0074-6624-90

Synthroid®

Levothyroxine
Sodium Tablets,
USP

100 mcg
(0.1 mg)

90 Tablets

Rx only abbvie